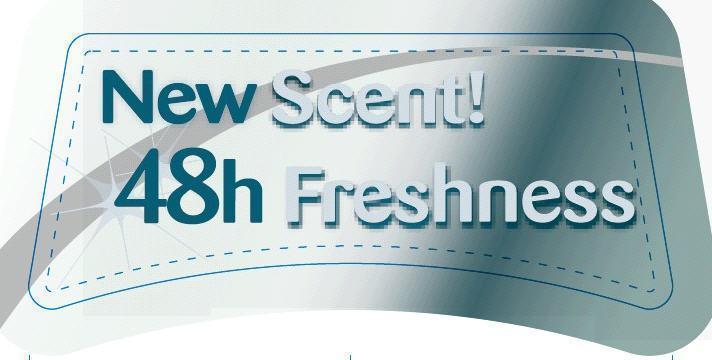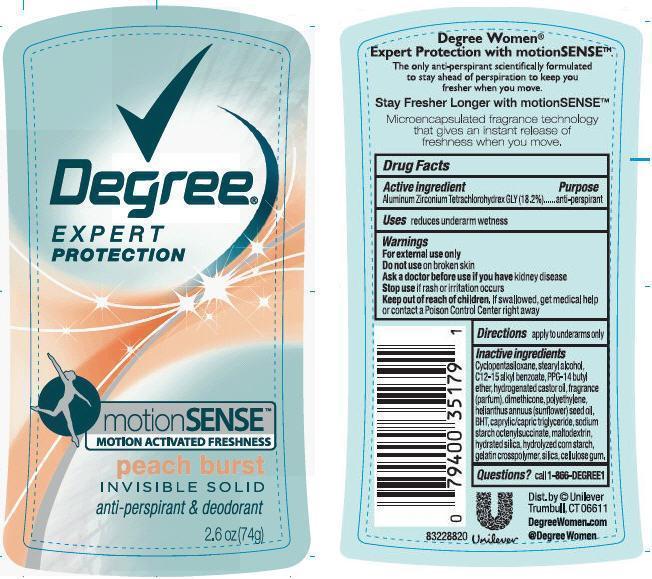 DRUG LABEL: Degree
NDC: 64942-1299 | Form: STICK
Manufacturer: Conopco Inc. d/b/a Unilever
Category: otc | Type: HUMAN OTC DRUG LABEL
Date: 20130516

ACTIVE INGREDIENTS: Aluminum Zirconium Tetrachlorohydrex GLY 18.2 g/100 g
INACTIVE INGREDIENTS: CYCLOMETHICONE 5; ALKYL (C12-15) BENZOATE; STEARYL ALCOHOL; HYDROGENATED CASTOR OIL; PPG-14 BUTYL ETHER; BUTYLATED HYDROXYTOLUENE; DIMETHICONE; SUNFLOWER OIL; MALTODEXTRIN; HYDRATED SILICA; SILICON DIOXIDE; CARBOXYMETHYLCELLULOSE SODIUM

Degree Expert Protection Motion Sense Peach Burst antiperspirant deodorant

Active Ingredient

Aluminum Zirconium Tetrachlorohydrex GLY (18.2%)

Purpose
anti-perspirant

INDICATIONS AND USAGE

Uses reduces underarm wetness

Warnings
For External Use Only

Do not use on broken skin

Ask a doctor before use if you have kidney disease

Stop use if rash or irritation occurs

Keep out of reach of children. If swallowed, get medical help or contact a Poison Control Center right away

DOSAGE AND ADMINISTRATION

Directionsapply to underarms only

Inactive ingredients

Cyclopentasiloxane, Stearyl Alcohol, C12-15 Alkyl Benzoate, PPG-14 Butyl Ether, Hydrogenated Castor Oil, Fragrance (Parfum), Dimethicone, Polyethylene, Helianthus Annuus (Sunflower) Seed Oil, BHT, Caprylic/Capric Triglyceride, Sodium Starch Octenylsuccinate, Maltodextrin, Hydrated Silica, Hydrolyzed Corn Starch, Gelatin Crosspolymer, Silica, Cellulose Gum.

Questions? Call 1-866-DEGREE1